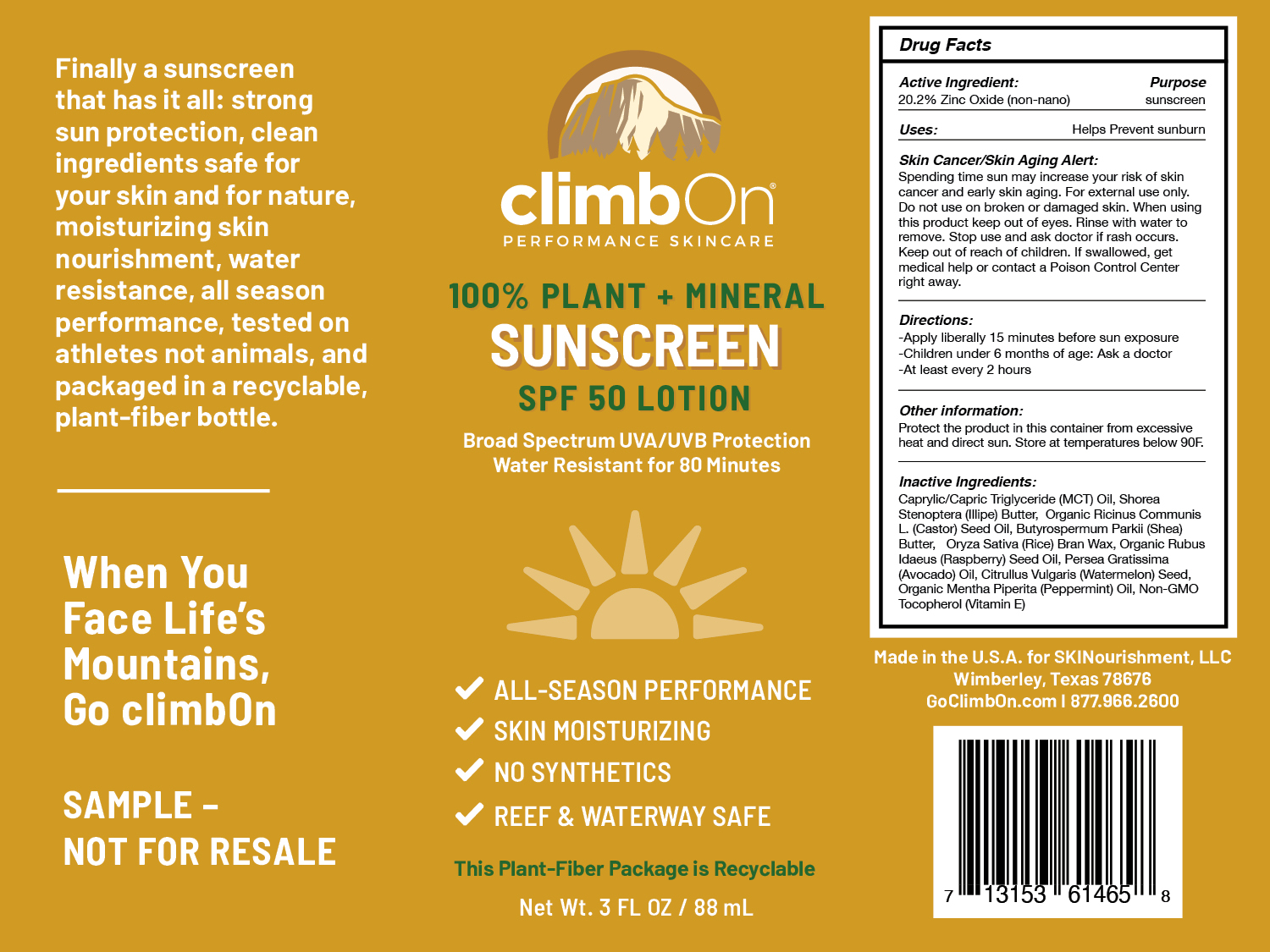 DRUG LABEL: PLANT AND MINERAL SUNSCREEN
NDC: 82233-101 | Form: LOTION
Manufacturer: SKINourishment, LLC.
Category: otc | Type: HUMAN OTC DRUG LABEL
Date: 20210913

ACTIVE INGREDIENTS: ZINC OXIDE 20.2 g/100 mL
INACTIVE INGREDIENTS: MEDIUM-CHAIN TRIGLYCERIDES; SHOREA STENOPTERA SEED BUTTER; CASTOR OIL; RICE BRAN; ORYZA SATIVA WHOLE; RUBUS IDAEUS SEED; AVOCADO OIL; WATERMELON SEED OIL; MENTHA PIPERITA; TOCOPHEROL

SKINourishment - PLANT AND MINERAL SUNSCREEN SPF 50

ACTIVE INGREDIENTS

20.2% ZINC OXIDE (non-nano)

PURPOSE

Sunscreen

USES

Helps prevent sunburn

Skin Cancer/Skin Aging Alert:

Spending time sun may increase your risk of skin cancer and ealry skin aging. For external use only. Do not use on broken or damaged skin. When using this product keep out of eyes. Rinse with water to remove. Stop use and ask a doctor if rash occurs.

Keep out of reach of children. If swallowed, get medical help or contact a Poison Control Center right away.

DIRECTIONS

- Apply liberally 15 minutes before sun exposure
- Children under 6 months of age: Ask a doctor
- At least every 2 hours

OTHER INFORMATION

- Protect this product in this container from excessive heat and direct sun. Sore at temperatures below 90F.

INACTIVE INGREDIENTS

Caprylic/Capric Triglyceride (MCT) Oil, Shorea Stenoptera (Illipe) Butter, Organic Ricinus Communis L. (Castor) Seed Oil, Butyrospermum Parkii (Shea) Butter, Oryza Sativa (Rice) Bran Wax, Organic Rubus Idaeus (Raspberry) Seed Oil, Persea Gratissima (Avocado) Oil, Citrullus Vulgaris (Watermelon) Seed, Organic Mentha Piperita (Peppermint) Oil, Non-GMO Tocopherol (Vitamin E)